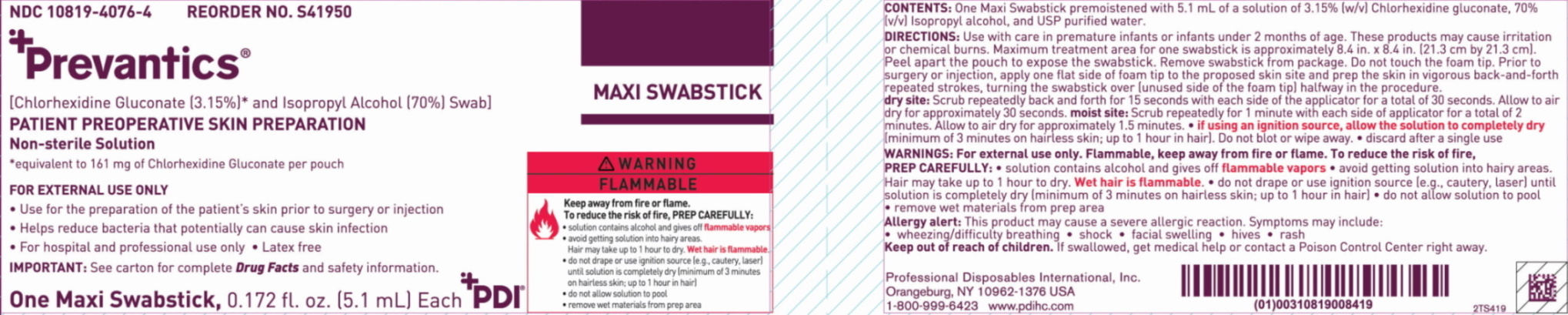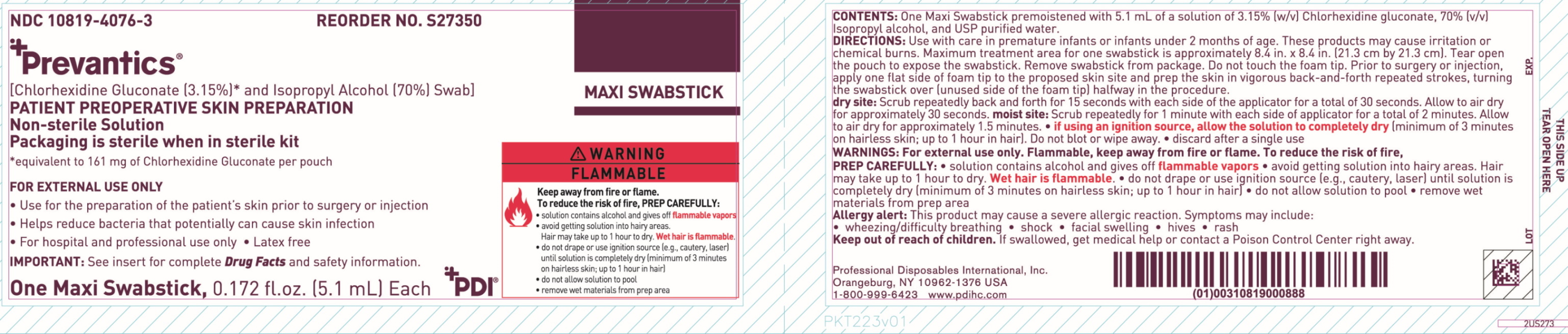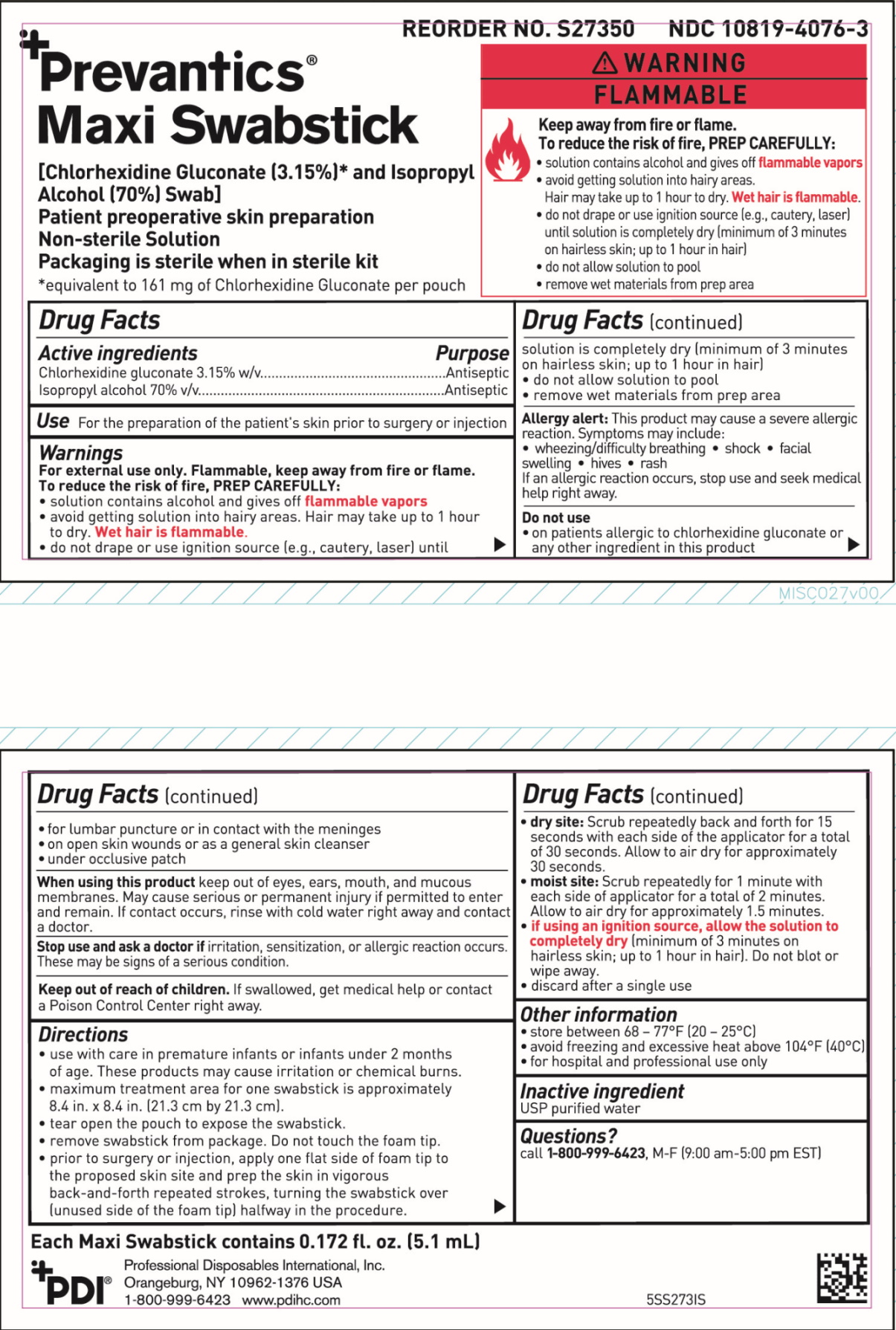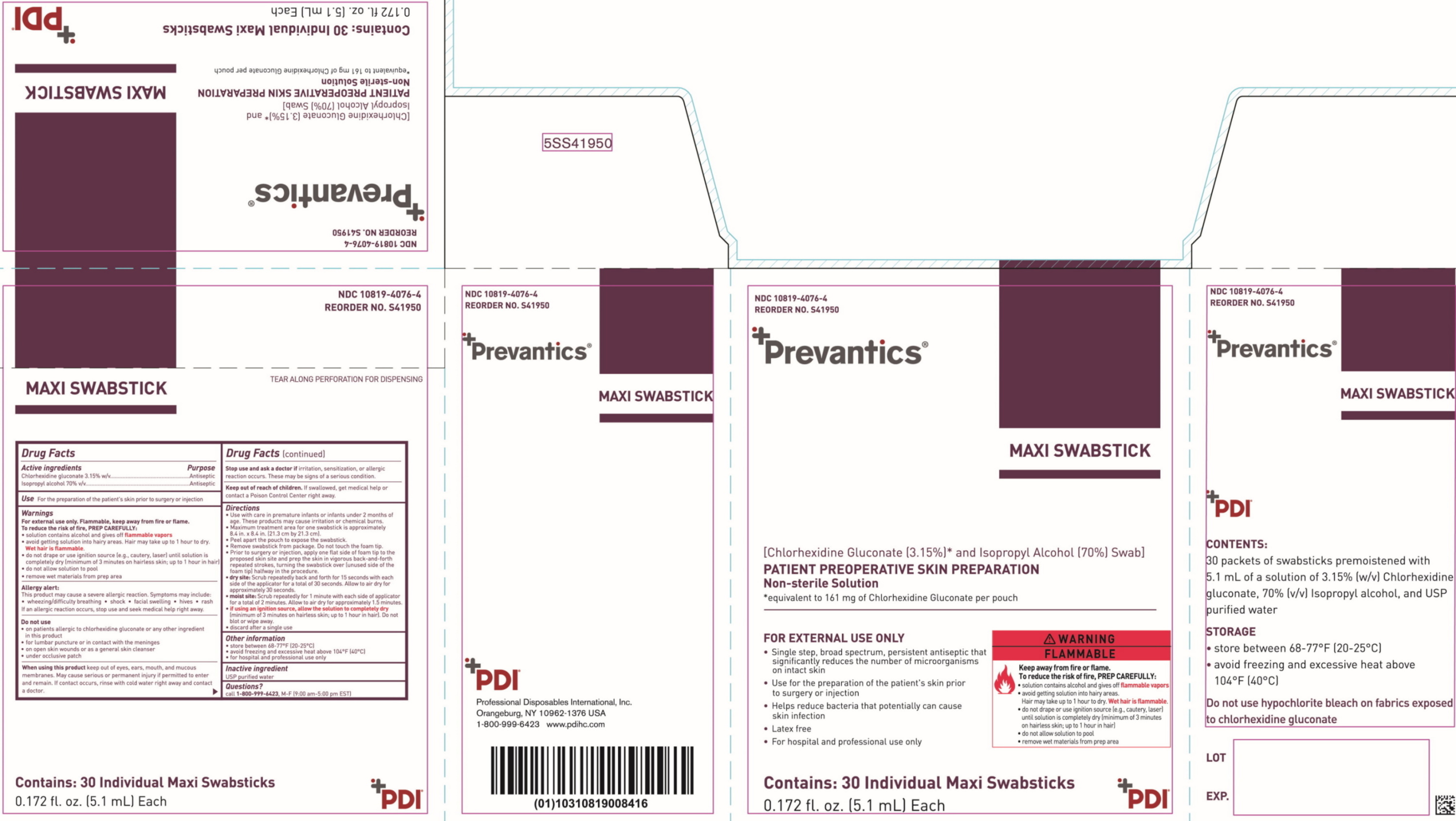 DRUG LABEL: Prevantics Maxi Swabstick
NDC: 10819-4076 | Form: SOLUTION
Manufacturer: Professional Disposables International, Inc.
Category: otc | Type: HUMAN OTC DRUG LABEL
Date: 20230630

ACTIVE INGREDIENTS: CHLORHEXIDINE GLUCONATE 31.5 mg/1 mL; ISOPROPYL ALCOHOL 0.7 mL/1 mL
INACTIVE INGREDIENTS: WATER

S27350- NDC 10819-4076-3
S41950- NDC-10819-4076-4

Active ingredients

Chlorhexidine gluconate 3.15% w/v

Isopropyl alcohol 70% v/v

Purposes

Antiseptic

Antiseptic

Use

for the preparation of the patient's skin prior to surgery or injection

Warnings

For external use only

Flammable, keep away from fire or flame

To reduce the risk of fire, PREP CAREFULLY:

- solution contains alcohol and gives off flammable vapors
- avoid getting solution into hairy areas. Hair may take up to 1 hour to dry. Wet hair is flammable.
- do not drape or use ignition source (e.g., cautery, laser) until solution is completely dry (minimum of 3 minutes on hairless skin; up to 1 hour in hair)
- do not allow solution to pool
- remove wet materials from prep area

Allergy alert

This product may cause a severe allergic reaction. Symptoms may include:

- wheezing/difficulty breathing
- shock
- facial swelling
- hives
- rash

If an allergic reaction occurs, stop use and seek medical help right away.

Do not use

- on patients allergic to chlorhexidine gluconate or any other ingredient in this product
- for lumbar puncture or in contact with the meninges
- on open skin wounds or as a general skin cleanser
- under occlusive patch

When using this product

keep out of eyes, ears, mouth and mucous membranes. May cause serious or permanent injury if permitted to enter and remain.

If contact occurs, rinse with cold water right away and contact a doctor.

Stop use and ask a doctor if

irritation, sensitization, or allergic reaction occurs. These may be signs of a serious condition.

Keep out of reach of children.

If swallowed, get medical help or contact a Poison Control Center right away.

Directions

- use with care in premature infants or infants under 2 months of age. These products may cause irritation or chemical burns.
- maximum treatment area for one swabstick is approximately 8.4 in. x 8.4 in. (21.3 cm by 21.3 cm).
- tear open the pouch to expose the swabstick
- remove swabstick from package. Do not touch the foam tip.
- prior to surgery or injection, apply one flat side of foam tip to the proposed skin site and prep the skin in vigorous back-and-forth repeated strokes, turning the swabstick over (unused side of the foam tip) halfway in the procedure
- dry site: scrub repeatedly back and forth for 15 seconds with each side of the applicator for a total of 30 seconds. Allow to air dry for approximately 30 seconds.
- moist site: scrub repeatedly for 1 minute with each side of the applicator for a total of 2 minutes. Allow to air dry for approximately 1.5 minutes.
- if using an ignition source, allow the solution to completely dry (minimum of 3 minutes on hairless skin; up to 1 hour in hair).
- do not blot or wipe away
- discard after a single use

Other information

- store between 68-77°F (20-25°C)
- avoid freezing and excessive heat above 104°F (40°C)
- for hospital and professional use only

Inactive ingredients

USP purified water

Package/Label Principal Display Panel

Prevantics(R) Maxi Swabstick
[Chlorhexidine Gluconate (3.15%)* and Isopropyl Alcohol (70%) Swab]
Patient preoperative skin preparation
Non-sterile solution

Packaging is sterile when in sterile kit

*equivalent to 161 mg of Chlorhexidine Gluconate per pouch

- For External Use Only
- Use for the preparation of the patient's skin prior to surgery or injection
- Helps reduce bacteria that potentially can cause skin infection
- For hospital and professional use only
- Latex free

IMPORTANT: See carton for complete Drug Factsand safety information.

Packet Label

Box Label

Packet (bulk):

Insert: